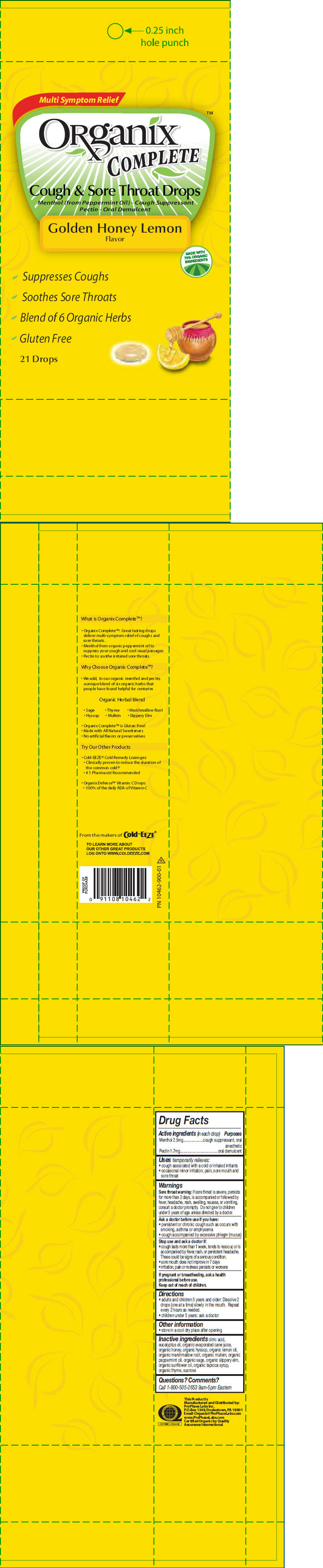 DRUG LABEL: Organix Complete
NDC: 61941-0122 | Form: LOZENGE
Manufacturer: ProPhase Labs, Inc.
Category: otc | Type: HUMAN OTC DRUG LABEL
Date: 20110406

ACTIVE INGREDIENTS: Menthol 2.5 mg/1 1; Pectin 1.7 mg/1 1
INACTIVE INGREDIENTS: Citric Acid Monohydrate; Eucalyptus Oil; Sucrose; Sage; Elm; Honey; Hyssop; Peppermint Oil; Lemon Oil; Sunflower Oil; Thyme

ORganix™
COMPLETE
Cough & Sore Throat Drops
Honey Lemon

Drug Facts

ACTIVE INGREDIENT

PURPOSE

Active ingredients (in each drop) | Purposes
Menthol 2.5mg | cough suppressant, oral anesthetic
Pectin 1.7mg | oral demulcent

Uses

temporarily relieves:

- cough associated with a cold or inhaled irritants
- occasional minor irritation, pain, sore mouth and sore throat

Warnings

Sore throat warning

if sore throat is severe, persists for more than 2 days, is accompanied or followed by fever, headache, rash, swelling, nausea, or vomiting, consult a doctor promptly. Do not give to children under 5 years of age unless directed by a doctor.

Ask a doctor before use if you have:

- persistent or chronic cough such as occurs with smoking, asthma or emphysema
- cough accompanied by excessive phlegm (mucus)

Stop use and ask a doctor if:

- cough lasts more than 1 week, tends to reoccur, or is accompanied by fever, rash, or persistent headache. These could be signs of a serious condition.
- sore mouth does not improve in 7 days
- irritation, pain or redness persists or worsens

PREGNANCY OR BREAST FEEDING

If pregnant or breastfeeding, ask a health professional before use.

Keep out of reach of children.

Directions

- adults and children 5 years and older: Dissolve 2 drops (one at a time) slowly in the mouth. Repeat every 2 hours as needed.
- children under 5 years: ask a doctor

Other information

- store in a cool dry place after opening

Inactive ingredients

citric acid, eucalyptus oil, organic evaporated cane juice, organic honey, organic hyssop, organic lemon oil, organic marshmallow root, organic mullein, organic peppermint oil, organic sage, organic slippery elm, organic sunflower oil, organic tapioca syrup, organic thyme, sucrose

Questions? Comments?

Call 1-800-505-2653 9am-5pm Eastern

PRINCIPAL DISPLAY PANEL - 21 Drop Package

Multi Symptom Relief

ORganix™
COMPLETE

Cough & Sore Throat Drops

Menthol (from Peppermint Oil) - Cough Suppressant
Pectin - Oral Demulcent

Golden Honey Lemon
Flavor

MADE WITH
70% ORGANIC
INGREDIENTS

Suppresses Coughs

Soothes Sore Throats

Blend of 6 Organic Herbs

Gluten Free

21 Drops